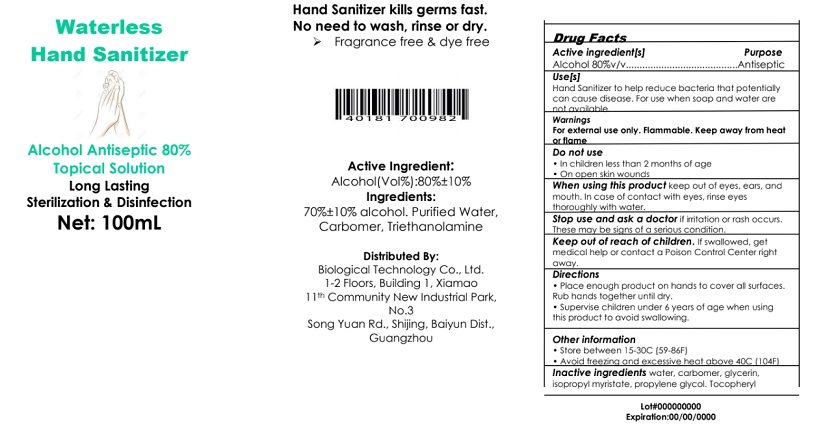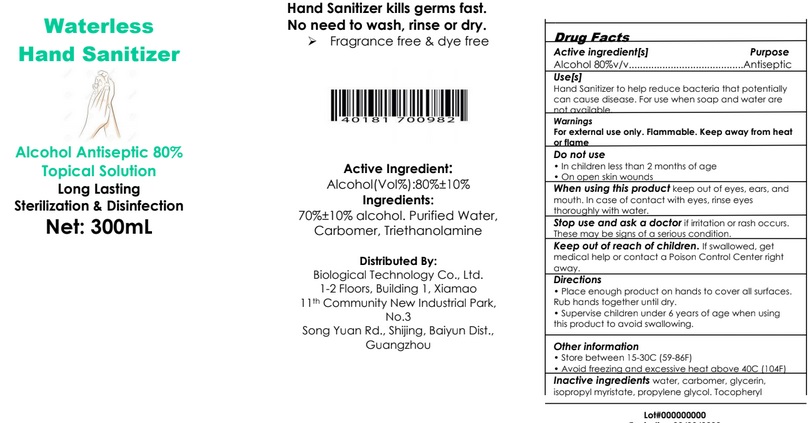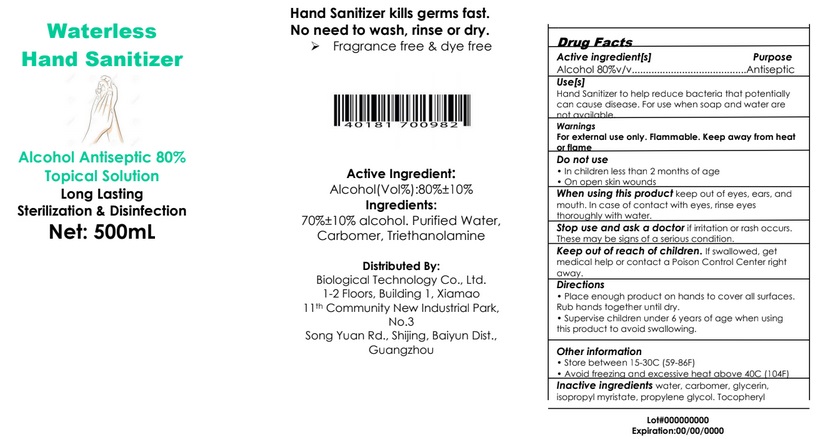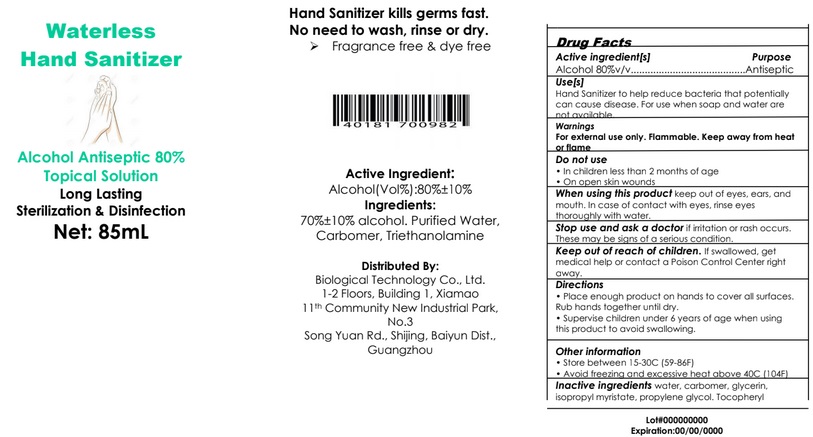 DRUG LABEL: Waterless hand sanitizer
NDC: 78933-001 | Form: GEL
Manufacturer: Genview corporation
Category: otc | Type: HUMAN OTC DRUG LABEL
Date: 20200616

ACTIVE INGREDIENTS: ALCOHOL 80 mL/100 mL
INACTIVE INGREDIENTS: WATER; CARBOMER HOMOPOLYMER, UNSPECIFIED TYPE; TROLAMINE

Active Ingredient

Alcohol 80% v/v.

Purpose

Antiseptic

Use

Hand Sanitizer to help reduce bacteria that potentially can cause disease. For use when soap and water are not available.

Warnings

For external use only. Flammable. Keep away from heat or flame.

Do not use in

- in children less than 2 months of age
- on open skin wounds

When using this product keep out of eyes, ears, and mouth. In case of contact with eyes, rinse eyes thoroughly with water.

Stop use and ask a doctor if irritation or rash occurs. These may be signs of a serious condition.

Keep out of reach of children. If swallowed, get medical help or contact a Poison Control Center right away.

Directions

- Place enough product on hands to cover all surfaces. Rub hands together until dry.
- Supervise children under 6 years of age when using this product to avoid swallowing.

Other information

- Store between 15-30^0C (59-86^0F).
- Avoid freezing and excessive heat above 40^0C (104^0F).

Inactive ingredients

Purified water, Carbomer, Triethanolamine.

Package Label - Principal Display Panel

Label 85 mL

Label 100 mL

Label 300 mL

Label 500 mL